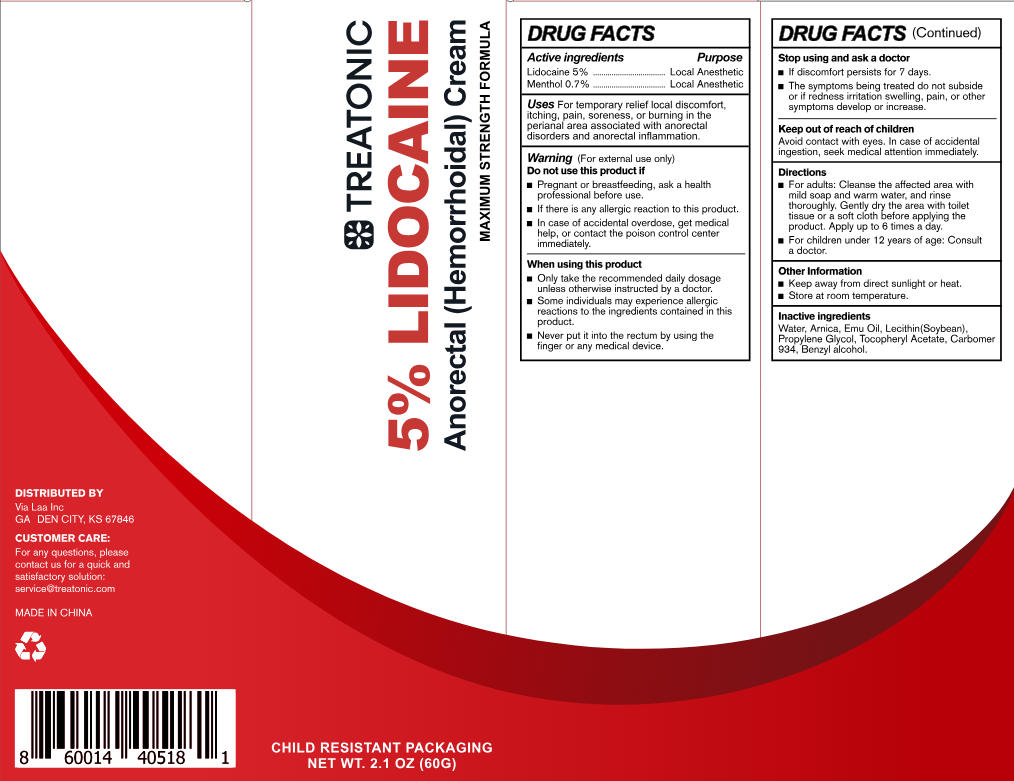 DRUG LABEL: Treatonic 5% Lidocaine Cream
NDC: 85569-012 | Form: CREAM
Manufacturer: 100 KARMA INC
Category: otc | Type: HUMAN OTC DRUG LABEL
Date: 20260108

ACTIVE INGREDIENTS: LIDOCAINE 3 g/60 g; MENTHOL 0.42 g/60 g
INACTIVE INGREDIENTS: LECITHIN, SOYBEAN; EMU OIL; CARBOMER 934; WATER; ARNICA MONTANA; ALPHA-TOCOPHEROL ACETATE; BENZYL ALCOHOL; PROPYLENE GLYCOL

Initial Drug Listing - Treatonic 5% Lidocaine Cream

ACTIVE INGREDIENT

Lidocaine 5%

Menthol 0.7%

PURPOSE

Local Anesthetic

DOSAGE AND ADMINISTRATION

For temporary relief local discomfort,itching,pain,soreness, or burning in the perianal area associated with anorectal isorders and anorectal inflammation.

WARNINGS

For external use only

DO NOT USE

- Pregnant or breastfeeding, ask a health professional before use.
- lf there is any allergic reaction to this product.
- In case of accidental overdose, get medical help, or contact the poison control center immediately.

WHEN USING

Only take the recommended daily dosage unless otherwise instructed by a doctor.

Some individuals may experience allergic reactions to the ingredients contained in this produet.
Never put it into the rectum by using the finger or any medical device.

ASK DOCTOR/PHARMACIST

- lf discomfort persists for 7 days.
- The symptoms being treated do not subside or if redness irritation swelling, pain, or other symptoms develop or increase.

KEEP OUT OF REACH OF CHILDREN

Avoid contact with eyes. In case of accidental ingestion, seek medical attention immediately.

INDICATIONS AND USAGE

- For adults: Cleanse the affected area with mild soap and warm water, and rinse thoroughly. Gently dry the area with toilet tissue or a soft cloth before applying theproduct. Apply up to 6 times a day.
- For children under 12 years of age: Consulta doctor.

OTHER SAFETY INFORMATION

- Keep away from direct sunlight or heat.
- Store at room temperature.

INACTIVE INGREDIENT

Water, Arnica, Emu Oil, Lecithin(Soybean),Propyiene Glycol, Tocopheryl Acetate, Carbomer 934, Benzyl alcohol.